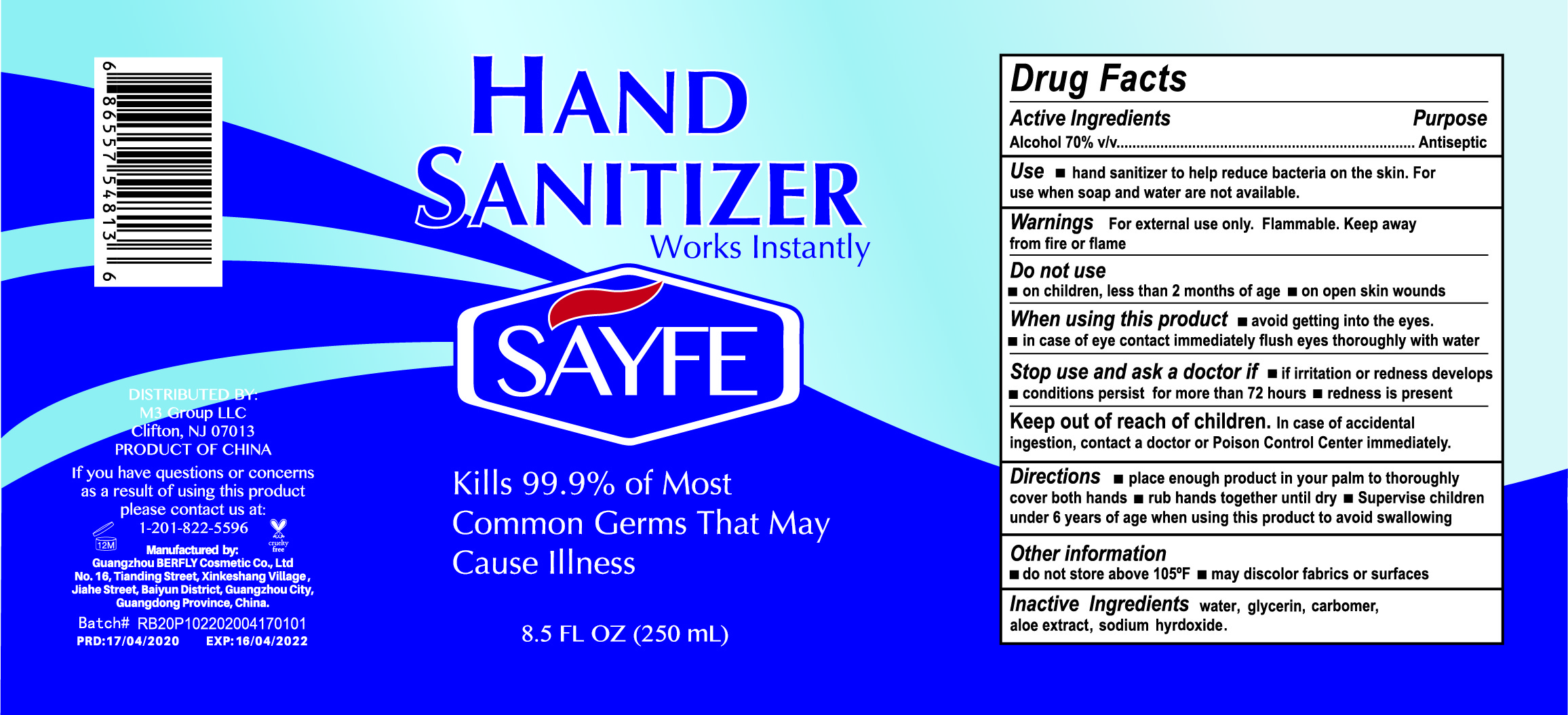 DRUG LABEL: Hand Sanitizer
NDC: 74176-001 | Form: SOLUTION
Manufacturer: M3 Group LLC
Category: otc | Type: HUMAN OTC DRUG LABEL
Date: 20200527

ACTIVE INGREDIENTS: ALCOHOL 70 mL/100 mL
INACTIVE INGREDIENTS: SODIUM HYDROXIDE; GLYCERIN; ALOE VERA LEAF; WATER; CARBOMER HOMOPOLYMER, UNSPECIFIED TYPE

Sayfe Hand Sanitizer

Active Ingredient

Alcohol 70% v/v

Purpose

Antiseptic

Use

■ hand sanitizer to help reduce bacteria on the skin. For use when soap and water are not available

Warnings

For external use only. Flammable. Keep away from fire or flame.

Do not use

■ in children less than 2 months of age ■ on open skin wounds

When using this product

■ avoid getting into the eyes. ■ in case of eye contact immediately flush eyes throughly with water

Stop use and ask a doctor if

■ irritation or redness develops ■ conditions persist for more than 72 hours ■ redness is present

Keep out of reach of children

In case of accidental ingestion, contact a doctor or Poison Control Center immediately.

Directions

■ place enough product in your palm to thoroughly cover both hands ■ rub hands together until dry ■ Supervise children under 6 years of age when using this product to avoid swallowing

Other information

■ do not store above 105ºF ■ may discolor fabrics or surfaces

Inactive Ingredients

water, glycerin, carbomer, aloe extract,sodium hydroxide